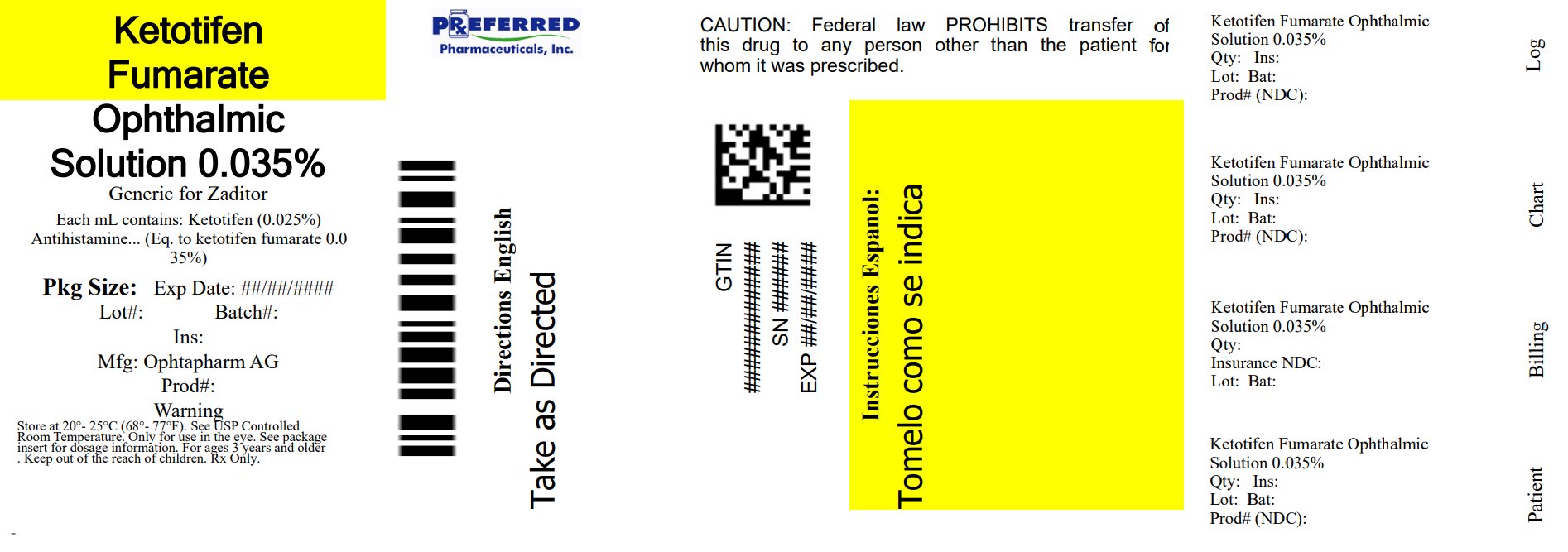 DRUG LABEL: Ketotifen Fumarate Ophthalmic Solution
NDC: 68788-4084 | Form: SOLUTION/ DROPS
Manufacturer: Preferred Pharmaceuticals Inc.
Category: otc | Type: HUMAN OTC DRUG LABEL
Date: 20260227

ACTIVE INGREDIENTS: KETOTIFEN FUMARATE 0.25 mg/1 mL
INACTIVE INGREDIENTS: BENZALKONIUM CHLORIDE; GLYCERIN; WATER; HYDROCHLORIC ACID; SODIUM HYDROXIDE

Ketotifen Fumarate Ophthalmic Solution

Drug Facts

Active ingredient

Ketotifen (0.025%)
(equivalent to Ketotifen Fumarate 0.035%)

Purpose

Antihistamine

Use

Temporarily relieves itchy eyes due to pollen, ragweed, grass, animal hair and dander.

Warnings

Do not use

- if solution changes color or becomes cloudy
- if you are sensitive to any ingredient in this product
- to treat contact lens related irritation

When using this product

- do not touch tip of container to any surface to avoid contamination
- remove contact lenses before use
- wait at least 10 minutes before reinserting contact lenses after use
- replace cap after each use

Stop use and ask a doctor if you experience any of the following:

- eye pain
- changes in vision
- redness of the eye
- itching worsens or lasts for more than 72 hours

Keep out of reach of children. If swallowed, get medical help or contact a Poison Control Center right away.

Directions

- Adults and children 3 years of age and older: Put 1 drop in the affected eye(s) twice daily, every 8-12 hours, no more than twice per day.
- Children under 3 years of age: Consult a doctor.

Other information

- Only for use in the eye.
- Store at 20° to 25°C (68° TO 77°F) [see USP Controlled Room Temperature].

Inactive ingredients

Benzalkonium Chloride 0.01%; Glycerin and Water for Injection. May contain Hydrochloric Acid and/or Sodium Hydroxide (to adjust pH).

Questions?

call toll-free 1-855-473-6847,weekdays, 7:00 AM - 5:30 PM CT

Now OTC!

ANTIHISTAMINE EYE DROPS

UPTO 12 HOURS EYE ITCH RELIEF

• Works in Minutes

• Original Prescription Strength

FOR AGES 3 YEARS AND OLDER
30 DAY SUPPLY

Sterile

Original Prescription Strength

Do not use if seal on bottle is missing or broken.

FOR TOPICAL OPHTHALMIC USE ONLY.

PRECAUTION: Do not touch dropper tip to any surface, as this may contaminate the solution.

Distributed by: Armas Pharmaceuticals, Inc.
Freehold, NJ 07728 (USA)

Manufactured by: Ophtapharm AG, Riethofstrasse 1,
Hettlingen, 8442, Switzerland (CHE) for Sentiss

Made in Switzerland

Relabeled By: Preferred Pharmaceuticals Inc.

NDC 68788-4084-5